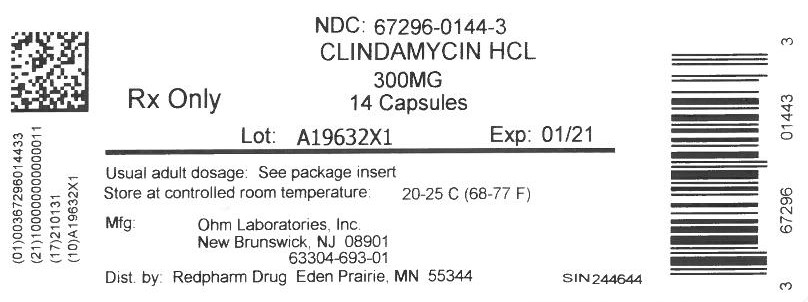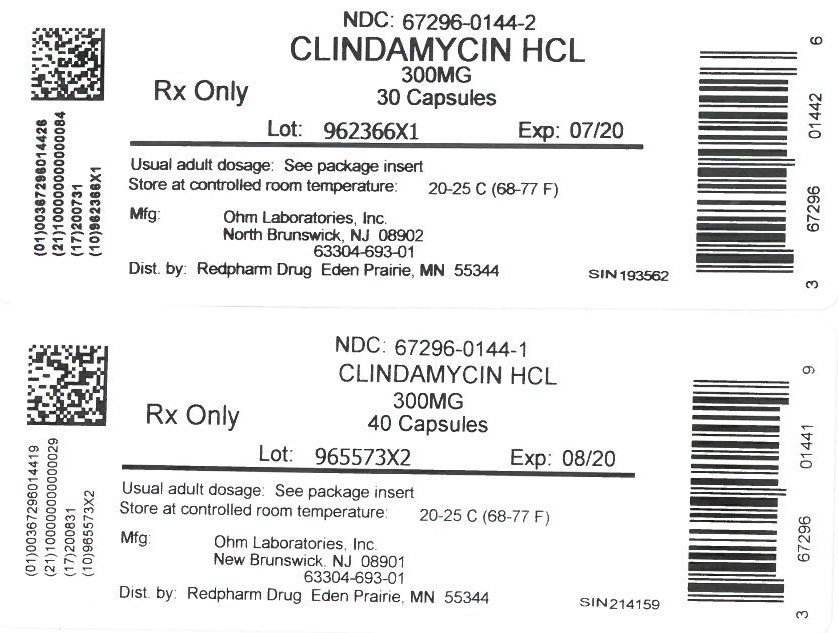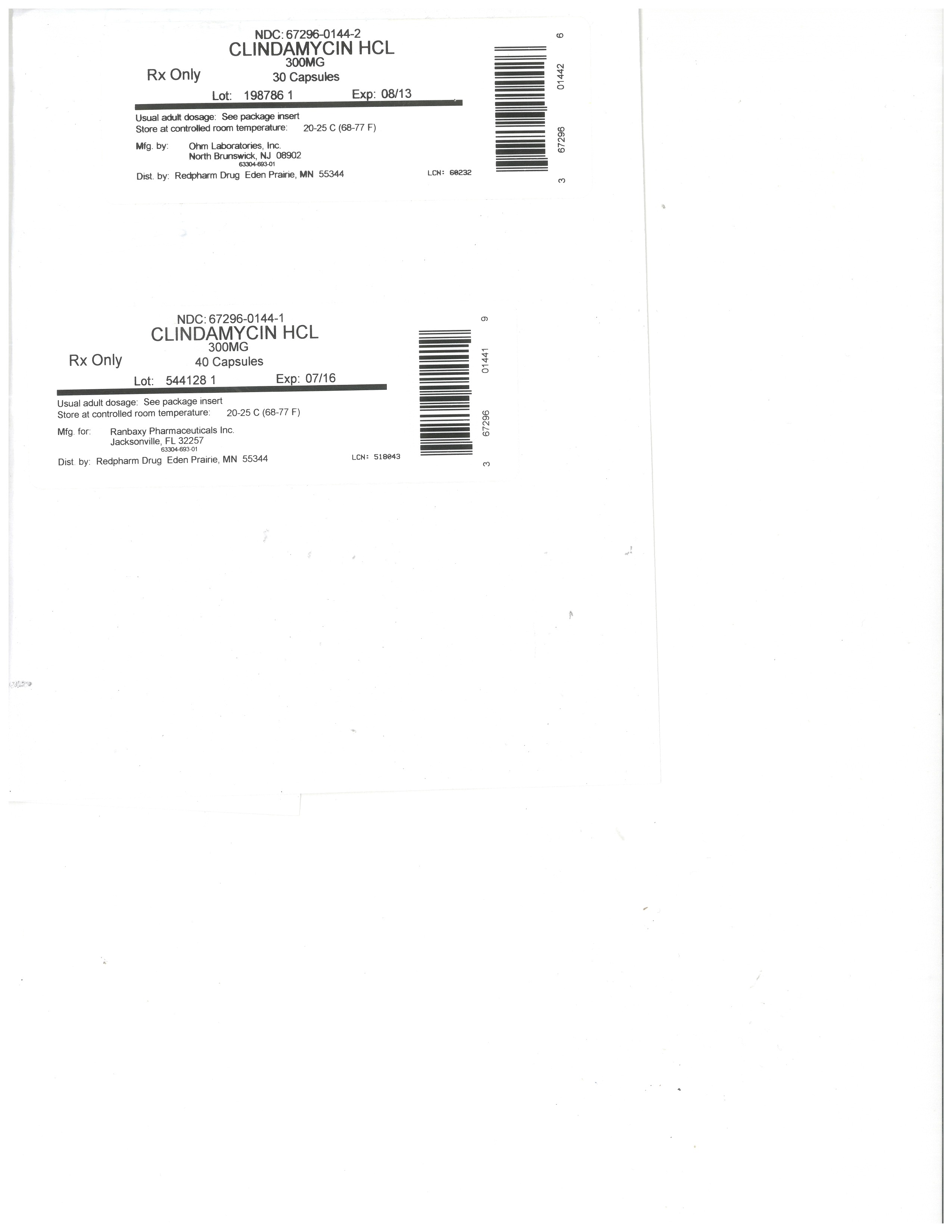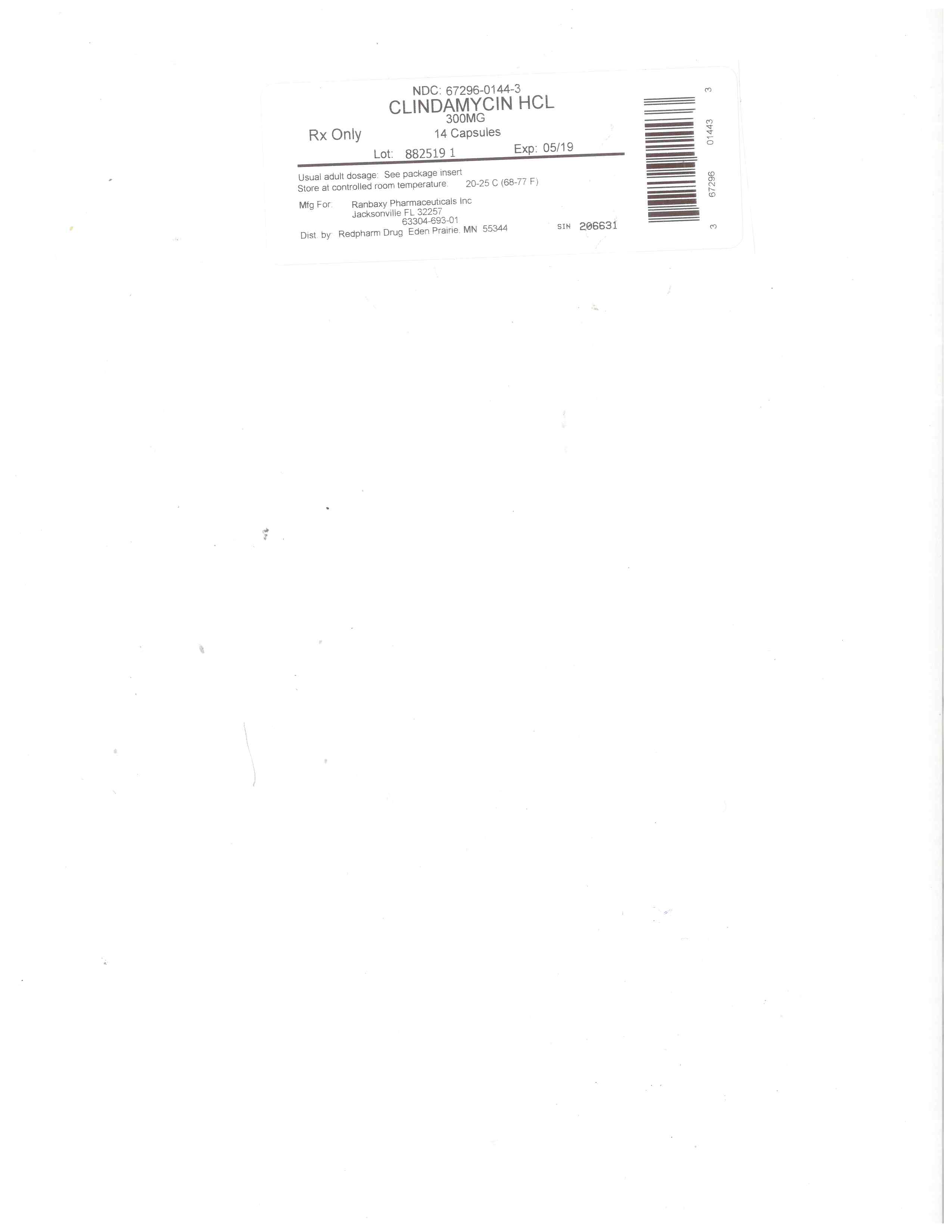 DRUG LABEL: Clindamycin hydrochloride
NDC: 67296-0144 | Form: CAPSULE
Manufacturer: RedPharm Drug, Inc.
Category: prescription | Type: HUMAN PRESCRIPTION DRUG LABEL
Date: 20240620

ACTIVE INGREDIENTS: CLINDAMYCIN HYDROCHLORIDE 300 mg/1 1
INACTIVE INGREDIENTS: SHELLAC; TALC; FERROSOFERRIC OXIDE; LACTOSE MONOHYDRATE; MAGNESIUM STEARATE; GELATIN; POTASSIUM HYDROXIDE; PROPYLENE GLYCOL; STARCH, CORN; TITANIUM DIOXIDE; FD&C BLUE NO. 1

BOXED WARNING

WARNING

Clostridium difficile associated diarrhea (CDAD) has been reported with use of nearly all antibacterial agents, including clindamycin hydrochloride and may range in severity from mild diarrhea to fatal colitis. Treatment with antibacterial agents alters the normal flora of the colon, leading to overgrowth of C. difficile.

Because clindamycin hydrochloride therapy has been associated with severe colitis which may end fatally, it should be reserved for serious infections where less toxic antimicrobial agents are inappropriate, as described in the INDICATIONS AND USAGE section. It should not be used in patients with nonbacterial infections such as most upper respiratory tract infections.

C. difficile produces toxins A and B, which contribute to the development of CDAD. Hypertoxin producing strains of C. difficile cause increased morbidity and mortality, as these infections can be refractory to antimicrobial therapy and may require colectomy. CDAD must be considered in all patients who present with diarrhea following antibiotic use. Careful medical history is necessary since CDAD has been reported to occur over two months after the administration of antibacterial agents.

If CDAD is suspected or confirmed, ongoing antibiotic use not directed against C. difficile may need to be discontinued. Appropriate fluid and electrolyte management, protein supplementation, antibiotic treatment of C. difficile, and surgical evaluation should be instituted as clinically indicated.

SPL UNCLASSIFIED SECTION

To reduce the development of drug-resistant bacteria and maintain the effectiveness of clindamycin hydrochloride capsules and other antibacterial drugs, clindamycin hydrochloride capsules should be used only to treat or prevent infections that are proven or strongly suspected to be caused by bacteria.

DESCRIPTION

Clindamycin hydrochloride is the hydrated hydrochloride salt of clindamycin. Clindamycin is a semisynthetic antibiotic produced by a 7(S)-chloro-substitution of the 7(R)-hydroxyl group of the parent compound lincomycin.

Clindamycin hydrochloride capsules, USP contain clindamycin hydrochloride, USP equivalent to 150 mg or 300 mg of clindamycin.

Inactive ingredients: 150 mg - black iron oxide, corn starch, D&C Yellow #10, FD&C Blue no. 1, gelatin, lactose monohydrate, magnesium stearate, potassium hydroxide, propylene glycol, shellac, talc, and titanium dioxide; 300 mg - black iron oxide, corn starch, FD&C Blue no. 1, gelatin, lactose monohydrate, magnesium stearate, potassium hydroxide, propylene glycol, shellac, talc, and titanium dioxide.

The structural formula is represented below:

[structure]

C18H33ClN2O5S•HCl M.W. 461.45

The chemical name for clindamycin hydrochloride is Methyl 7-chloro-6, 7, 8-trideoxy-6-(1-methyl-trans-4-propyl-L-2-pyrrolidinecarboxamido)-1-thio-L-threo-α-D-galacto-octopyranoside monohydrochloride.

CLINICAL PHARMACOLOGY

Human Pharmacology

Absorption

Serum level studies with a 150 mg oral dose of clindamycin hydrochloride in 24 normal adult volunteers showed that clindamycin was rapidly absorbed after oral administration. An average peak serum level of 2.50 mcg/mL was reached in 45 minutes; serum levels averaged 1.51 mcg/mL at 3 hours and 0.70 mcg/mL at 6 hours. Absorption of an oral dose is virtually complete (90%), and the concomitant administration of food does not appreciably modify the serum concentrations; serum levels have been uniform and predictable from person to person and dose to dose. Serum level studies following multiple doses of clindamycin hydrochloride for up to 14 days show no evidence of accumulation or altered metabolism of drug. Doses of up to 2 grams of clindamycin per day for 14 days have been well tolerated by healthy volunteers, except that the incidence of gastrointestinal side effects is greater with the higher doses.

Distribution

Concentrations of clindamycin in the serum increased linearly with increased dose. Serum levels exceed the MIC (minimum inhibitory concentration) for most indicated organisms for at least six hours following administration of the usually recommended doses. Clindamycin is widely distributed in body fluids and tissues (including bones). No significant levels of clindamycin are attained in the cerebrospinal fluid, even in the presence of inflamed meninges.

Excretion

The average biological half-life is 2.4 hours. Approximately 10% of the bioactivity is excreted in the urine and 3.6% in the feces; the remainder is excreted as bioinactive metabolites.

Special Populations

Renal Impairment

Serum half-life of clindamycin is increased slightly in patients with markedly reduced renal function. Hemodialysis and peritoneal dialysis are not effective in removing clindamycin from the serum.

Use in Elderly

Pharmacokinetic studies in elderly volunteers (61 to 79 years) and younger adults (18 to 39 years) indicate that age alone does not alter clindamycin pharmacokinetics (clearance, elimination half-life, volume of distribution, and area under the serum concentration-time curve) after IV administration of clindamycin phosphate. After oral administration of clindamycin hydrochloride, elimination half-life is increased to approximately 4 hours (range 3.4 to 5.1 h) in the elderly compared to 3.2 hours (range 2.1 to 4.2 h) in younger adults. The extent of absorption, however, is not different between age groups and no dosage alteration is necessary for the elderly with normal hepatic function and normal (age-adjusted) renal function.

Microbiology

Clindamycin inhibits bacterial protein synthesis by binding to the 50S subunit of the ribosome. It has activity against Gram-positive aerobes and anaerobes as well as some Gram-negative anaerobes. Clindamycin is bacteriostatic. Cross-resistance between clindamycin and lincomycin is complete. Antagonism in vitro has been demonstrated between clindamycin and erythromycin. Clindamycin inducible resistance has been identified in macrolide-resistant staphylococci and beta-hemolytic streptococci. Macrolide-resistant isolates of these organisms should be screened for clindamycin inducible resistance using the D-zone test.

Clindamycin has been shown to be active against most of the isolates of the following microorganisms, both in vitro and in clinical infections, as described in the INDICATIONS AND USAGE section.

Gram-positive aerobes

Staphylococcus aureus (methicillin-susceptible strains)

Streptococcus pneumoniae (penicillin-susceptible strains)

Streptococcus pyogenes

Anaerobes

Prevotella melaninogenica

Fusobacterium necrophorum

Fusobacterium nucleatum

Peptostreptococcus anaerobius

Clostridium perfringens

At least 90% of the microorganisms listed below exhibit in vitro minimum inhibitory concentrations (MICs) less than or equal to the clindamycin susceptible MIC breakpoint for organisms of a similar type to those shown in Table 1. However, the efficacy of clindamycin in treating clinical infections due to these microorganisms has not been established in adequate and well-controlled clinical trials.

Gram-positive aerobes

Staphylococcus epidermidis (methicillin-susceptible strains)

Streptococcus agalactiae

Streptococcus anginosus

Streptococcus oralis

Streptococcus mitis

Anaerobes

Prevotella intermedia

Prevotella bivia

Propionibacterium acnes

Micromonas (“Peptostreptococcus”) micros

Finegoldia (“Peptostreptococcus”) magna

Actinomyces israelii

Clostridium clostridioforme

Eubacterium lentum

Susceptibility Testing Methods

When available, the clinical microbiology laboratory should provide cumulative in vitro susceptibility test results for antimicrobial drugs used in local hospitals and practice areas to the physician as periodic reports that describe the susceptibility profile of nosocomial and community-acquired pathogens. These reports should aid the physician in selecting the most effective antimicrobial.

Dilution Techniques

Quantitative methods are used to determine antimicrobial minimum inhibitory concentrations (MICs). These MICs provide estimates of the susceptibility of bacteria to antimicrobial compounds. The MICs should be determined using a standardized procedure based on dilution method (broth, agar, or microdilution)1,2 or equivalent using standardized inoculum and concentrations of clindamycin. The MIC values should be interpreted according to the criteria provided in Table 1.

Diffusion Techniques

Quantitative methods that require the measurement of zone diameters also provide reproducible estimates of the susceptibility of bacteria to antimicrobial compounds. The standardized procedure1,3requires the use of standardized inoculum concentrations. This procedure uses paper disks impregnated with 2 mcg of clindamycin to test the susceptibility of microorganisms to clindamycin. Reports from the laboratory providing results of the standard single-disk susceptibility test with a 2 mcg clindamycin disk should be interpreted according to the criteria in Table 1.

Table 1. Susceptibility Interpretive Criteria for Clindamycin
Pathogen Susceptibility Interpretive Criteria
Minimal Inhibitory Concentrations (MIC in mcg/mL) Disk Diffusion (Zone Diameters in mm)
S I R S I R
Staphylococcus spp. ≤ 0.5 1 to 2 ≥ 4 ≥ 21 15 to 20 ≤ 14
Streptococcus pneumoniaeand other Streptococcusspp. ≤ 0.25 0.5 ≥ 1 ≥ 19 16 to 18 ≤ 15
Anaerobic Bacteria ≤ 2 4 ≥ 8 NA NA NA

NA = not applicable

A report of “Susceptible” indicates that the pathogen is likely to be inhibited if the antimicrobial compound in the blood reaches the concentrations usually achievable. A report of “Intermediate” indicates that the result should be considered equivocal, and, if the microorganism is not fully susceptible to alternative, clinically feasible drugs, the test should be repeated. This category implies possible clinical applicability in body sites where the drug is physiologically concentrated or in situations where high dosage of drug can be used. This category also provides a buffer zone that prevents small, uncontrolled technical factors from causing major discrepancies in interpretation.

A report of “Resistant” indicates that the pathogen is not likely to be inhibited if the antimicrobial compound in the blood reaches the concentrations usually achievable; other therapy should be selected.

Quality Control

Standardized susceptibility test procedures require the use of laboratory controls to monitor and ensure the accuracy and precision of the supplies and reagents used in the assay, and the techniques of the individuals performing the test.1,2,3,4 Standard clindamycin powder should provide the MIC ranges in Table 2. For the disk diffusion technique using the 2 mcg clindamycin disk the criteria provided in Table 2 should be achieved.

Table 2. Acceptable Quality Control Ranges for Clindamycin to be Used in Validation of Susceptibility Test Results
Acceptable Quality Control Ranges
QC Strain Minimum Inhibitory Concentration Range(mcg/mL) Disk Diffusion Range(Zone Diameters in mm)
When Testing Aerobic Pathogens
Staphylococcus aureus ATCC 29213 0.06 to 0.25 NA
Staphylococcus aureus ATCC 25923 NA 24 to 30
Streptococcus pneumoniae ATCC 49619 0.03 to 0.12 19 to 25
When Testing Anaerobes
Bacteroides fragilis ATCC 25285 0.5 to 2 NA
Bacteroides thetaiotaomicron ATCC 29741 2 to 8 NA
Eubacterium lentum ATCC 43055 0.06 to 0.25 NA

NA = Not applicable

ATCC® is a registered trademark of the American Type Culture Collection

INDICATIONS AND USAGE

Clindamycin hydrochloride capsules, USP are indicated in the treatment of serious infections caused by susceptible anaerobic bacteria.

Clindamycin hydrochloride capsules, USP are also indicated in the treatment of serious infections due to susceptible strains of streptococci, pneumococci, and staphylococci. Its use should be reserved for penicillin-allergic patients or other patients for whom, in the judgment of the physician, a penicillin is inappropriate. Because of the risk of colitis, as described in the WARNING box, before selecting clindamycin hydrochloride capsules, USP are the physician should consider the nature of the infection and the suitability of less toxic alternatives (e.g., erythromycin).

Anaerobes: Serious respiratory tract infections such as empyema, anaerobic pneumonitis, and lung abscess; serious skin and soft tissue infections; septicemia; intra-abdominal infections such as peritonitis and intra-abdominal abscess (typically resulting from anaerobic organisms resident in the normal gastrointestinal tract); infections of the female pelvis and genital tract such as endometritis, nongonococcal tubo-ovarian abscess, pelvic cellulitis, and postsurgical vaginal cuff infection.

Streptococci: Serious respiratory tract infections; serious skin and soft tissue infections.

Staphylococci: Serious respiratory tract infections; serious skin and soft tissue infections.

Pneumococci: Serious respiratory tract infections.

Bacteriologic studies should be performed to determine the causative organisms and their susceptibility to clindamycin.

To reduce the development of drug-resistant bacteria and maintain the effectiveness of clindamycin hydrochloride capsules, USP and other antibacterial drugs, clindamycin hydrochloride capsules, USP should be used only to treat or prevent infections that are proven or strongly suspected to be caused by susceptible bacteria. When culture and susceptibility information are available, they should be considered in selecting or modifying antibacterial therapy. In the absence of such data, local epidemiology and susceptibility patterns may contribute to the empiric selection of therapy.

CONTRAINDICATIONS

Clindamycin hydrochloride capsules are contraindicated in individuals with a history of hypersensitivity to preparations containing clindamycin or lincomycin.

WARNINGS

See WARNING box.

Clostridium difficile associated diarrhea (CDAD) has been reported with use of nearly all antibacterial agents, including clindamycin hydrochloride, and may range in severity from mild diarrhea to fatal colitis. Treatment with antibacterial agents alters the normal flora of the colon, leading to overgrowth of C. difficile.

C. difficile produces toxins A and B, which contribute to the development of CDAD. Hypertoxin producing strains of C. difficile cause increased morbidity and mortality, as these infections can be refractory to antimicrobial therapy and may require colectomy. CDAD must be considered in all patients who present with diarrhea following antibiotic use. Careful medical history is necessary since CDAD has been reported to occur over two months after the administration of antibacterial agents.

If CDAD is suspected or confirmed, ongoing antibiotic use not directed against C. difficile may need to be discontinued. Appropriate fluid and electrolyte management, protein supplementation, antibiotic treatment of C. difficile, and surgical evaluation should be instituted as clinically indicated.

A careful inquiry should be made concerning previous sensitivities to drugs and other allergens.

Usage in Meningitis-Since clindamycin does not diffuse adequately into the cerebrospinal fluid, the drug should not be used in the treatment of meningitis.

PRECAUTIONS

General

Review of experience to date suggests that a subgroup of older patients with associated severe illness may tolerate diarrhea less well. When clindamycin is indicated in these patients, they should be carefully monitored for change in bowel frequency.

Clindamycin hydrochloride should be prescribed with caution in individuals with a history of gastrointestinal disease, particularly colitis.

Clindamycin hydrochloride should be prescribed with caution in atopic individuals.

Indicated surgical procedures should be performed in conjunction with antibiotic therapy.

The use of clindamycin hydrochloride occasionally results in overgrowth of nonsusceptible organisms—particularly yeasts. Should superinfections occur, appropriate measures should be taken as indicated by the clinical situation.

Clindamycin dosage modification may not be necessary in patients with renal disease. In patients with moderate to severe liver disease, prolongation of clindamycin half-life has been found. However, it was postulated from studies that when given every eight hours, accumulation should rarely occur. Therefore, dosage modification in patients with liver disease may not be necessary. However, periodic liver enzyme determinations should be made when treating patients with severe liver disease.

Prescribing clindamycin hydrochloride capsules in the absence of a proven or strongly suspected bacterial infection or a prophylactic indication is unlikely to provide benefit to the patient and increases the risk of the development of drug-resistant bacteria.

Information for Patients

Patients should be counseled that antibacterial drugs, including clindamycin hydrochloride capsules, should only be used to treat bacterial infections. They do not treat viral infections (e.g., the common cold). When clindamycin hydrochloride capsules are prescribed to treat a bacterial infection, patients should be told that although it is common to feel better early in the course of therapy, the medication should be taken exactly as directed. Skipping doses or not completing the full course of therapy may (1) decrease the effectiveness of the immediate treatment and (2) increase the likelihood that bacteria will develop resistance and will not be treatable by clindamycin hydrochloride capsules or other antibacterial drugs in the future.

Diarrhea is a common problem caused by antibiotics which usually ends when the antibiotic is discontinued. Sometimes after starting treatment with antibiotics, patients can develop watery and bloody stools (with or without stomach cramps and fever) even as late as two or more months after having taken the last dose of the antibiotic. If this occurs, patients should contact their physician as soon as possible.

Laboratory Tests

During prolonged therapy, periodic liver and kidney function tests and blood counts should be performed.

Drug Interactions

Clindamycin has been shown to have neuromuscular blocking properties that may enhance the action of other neuromuscular blocking agents. Therefore, it should be used with caution in patients receiving such agents.

Antagonism has been demonstrated between clindamycin and erythromycin in vitro. Because of possible clinical significance, these two drugs should not be administered concurrently.

Carcinogenesis, Mutagenesis, Impairment of Fertility

Long-term studies in animals have not been performed with clindamycin to evaluate carcinogenic potential. Genotoxicity tests performed included a rat micronucleus test and an Ames Salmonella reversion test. Both tests were negative.

Fertility studies in rats treated orally with up to 300 mg/kg/day (approximately 1.6 times the highest recommended adult human dose based on mg/m2) revealed no effects on fertility or mating ability.

Pregnancy: Teratogenic effects

Pregnancy Category B

Reproduction studies performed in rats and mice using oral doses of clindamycin up to 600 mg/kg/day (3.2 and 1.6 times the highest recommended adult human dose based on mg/m2, respectively) or subcutaneous doses of clindamycin up to 250 mg/kg/day (1.3 and 0.7 times the highest recommended adult human dose based on mg/m2, respectively) revealed no evidence of teratogenicity.

There are, however, no adequate and well-controlled studies in pregnant women. Because animal reproduction studies are not always predictive of the human response, this drug should be used during pregnancy only if clearly needed.

Nursing Mothers

Clindamycin has been reported to appear in breast milk in the range of 0.7 to 3.8 mcg/mL.

Pediatric Use

When clindamycin hydrochloride is administered to the pediatric population (birth to 16 years), appropriate monitoring of organ system functions is desirable.

Geriatric Use

Clinical studies of clindamycin did not include sufficient numbers of patients age 65 and over to determine whether they respond differently from younger patients. However, other reported clinical experience indicates that antibiotic-associated colitis and diarrhea (due to Clostridium difficile) seen in association with most antibiotics occur more frequently in the elderly (> 60 years) and may be more severe. These patients should be carefully monitored for the development of diarrhea.

Pharmacokinetic studies with clindamycin have shown no clinically important differences between young and elderly subjects with normal hepatic function and normal (age-adjusted) renal function after oral or intravenous administration.

ADVERSE REACTIONS

The following reactions have been reported with the use of clindamycin.

Gastrointestinal: Abdominal pain, pseudomembranous colitis, esophagitis, nausea, vomiting, and diarrhea (see WARNING box). The onset of pseudomembranous colitis symptoms may occur during or after antibacterial treatment (see WARNINGS).

HypersensitivityReactions: Generalized mild to moderate morbilliform-like (maculopapular) skin rashes are the most frequently reported adverse reactions. Vesiculobullous rashes, as well as urticaria, have been observed during drug therapy. Rare instances of erythema multiforme, some resembling Stevens-Johnson syndrome, and a few cases of anaphylactoid reactions have also been reported.

Skin and Mucous Membranes: Pruritus, vaginitis, and rare instances of exfoliative dermatitis have been reported. (See Hypersensitivity Reactions.)

Liver: Jaundice and abnormalities in liver function tests have been observed during clindamycin therapy.

Renal: Although no direct relationship of clindamycin to renal damage has been established, renal dysfunction as evidenced by azotemia, oliguria, and/or proteinuria has been observed in rare instances.

Hematopoietic: Transient neutropenia (leukopenia) and eosinophilia have been reported. Reports of agranulocytosis and thrombocytopenia have been made. No direct etiologic relationship to concurrent clindamycin therapy could be made in any of the foregoing.

Musculoskeletal: Rare instances of polyarthritis have been reported.

OVERDOSAGE

Significant mortality was observed in mice at an intravenous dose of 855 mg/kg and in rats at an oral or subcutaneous dose of approximately 2618 mg/kg. In the mice, convulsions and depression were observed.

Hemodialysis and peritoneal dialysis are not effective in removing clindamycin from the serum.

DOSAGE AND ADMINISTRATION

If significant diarrhea occurs during therapy, this antibiotic should be discontinued (see WARNING box).

Adults: Serious infections—150 to 300 mg every 6 hours. More severe infections - 300 to 450 mg every 6 hours. Pediatric Patients: Serious infections - 8 to 16 mg/kg/day (4 to 8 mg/lb/day) divided into three or four equal doses. More severe infections - 16 to 20 mg/kg/day (8 to 10 mg/lb/day) divided into three or four equal doses.

To avoid the possibility of esophageal irritation, clindamycin hydrochloride capsules should be taken with a full glass of water.

Serious infections due to anaerobic bacteria are usually treated with clindamycin injection. However, in clinically appropriate circumstances, the physician may elect to initiate treatment or continue treatment with clindamycin hydrochloride capsules.

In cases of β-hemolytic streptococcal infections, treatment should continue for at least 10 days.

HOW SUPPLIED

Clindamycin hydrochloride capsules, USP are available in the following strengths, colors and sizes:

Clindamycin hydrochloride capsules, USP, 150 mg are size ‘1’ capsules with turquoise blue opaque cap and light green body imprinted with “RX692” on cap and body in black ink containing white to off white powder. They are supplied as follows:

NDC 63304-692-01 Bottles of 100

NDC 63304-692-05 Bottles of 500

NDC 63304-692-77 Blister of 100

Clindamycin hydrochloride capsules, USP, 300 mg are size ‘0’ capsules with turquoise blue opaque cap and turquoise blue opaque body imprinted with “RX693” on cap and body in black ink containing white to off white powder. They are supplied as follows:

NDC 63304-693-16 Bottles of 16

NDC 63304-693-01 Bottles of 100

NDC 63304-693-77 Blister of 100

Store at 20° - 25° C (68° - 77° F) [See USP Controlled Room Temperature].

TO report SUSPECTED ADVERSE REACTIONS, contact the FDA at 1-800-FDA-1088 or www.fda.gov/medwatch.

ANIMAL TOXICOLOGY

One-year oral toxicity studies in Spartan Sprague-Dawley rats and beagle dogs at dose levels up to 300 mg/kg/day (approximately 1.6 and 5.4 times the highest recommended adult human dose based on mg/m2, respectively) have shown clindamycin to be well tolerated. No appreciable difference in pathological findings has been observed between groups of animals treated with clindamycin and comparable control groups. Rats receiving clindamycin hydrochloride at 600 mg/kg/day (approximately 3.2 times the highest recommended adult human dose based on mg/m2) for 6 months tolerated the drug well; however, dogs dosed at this level (approximately 10.8 times the highest recommended adult human dose based on mg/m2) vomited, would not eat, and lost weight.

REFERENCES

CLSI. Performance Standards for Antimicrobial Susceptibility Testing: Twentieth Informational Supplement. CLSI document M 100-S20. Wayne, PA: Clinical and Laboratory Standards Institute; 2010.
CLSI. Methods for Dilution Antimicrobial Susceptibility Tests for Bacteria that Grow Aerobically; Approved Standard– Eighth Edition. CLSI document M07-A8. Wayne, PA: Clinical and Laboratory Standards Institute; 2009.
CLSI. Performance Standards for Antimicrobial Disk Susceptibility Tests; Approved Standard - Tenth Edition. CLSI document M02-A10. Wayne, PA: Clinical and Laboratory Standards Institute; 2009.
CLSI. Methods for Antimicrobial Susceptibility Testing of Anaerobic Bacteria; Approved Standard-Seventh Edition. CLSI document M11-A7. Wayne, PA: Clinical and Laboratory Standards Institute; 2007.

Manufactured for:

Ranbaxy Pharmaceuticals Inc.

Jacksonville, FL 32257 USA

March 2013 FDA-05